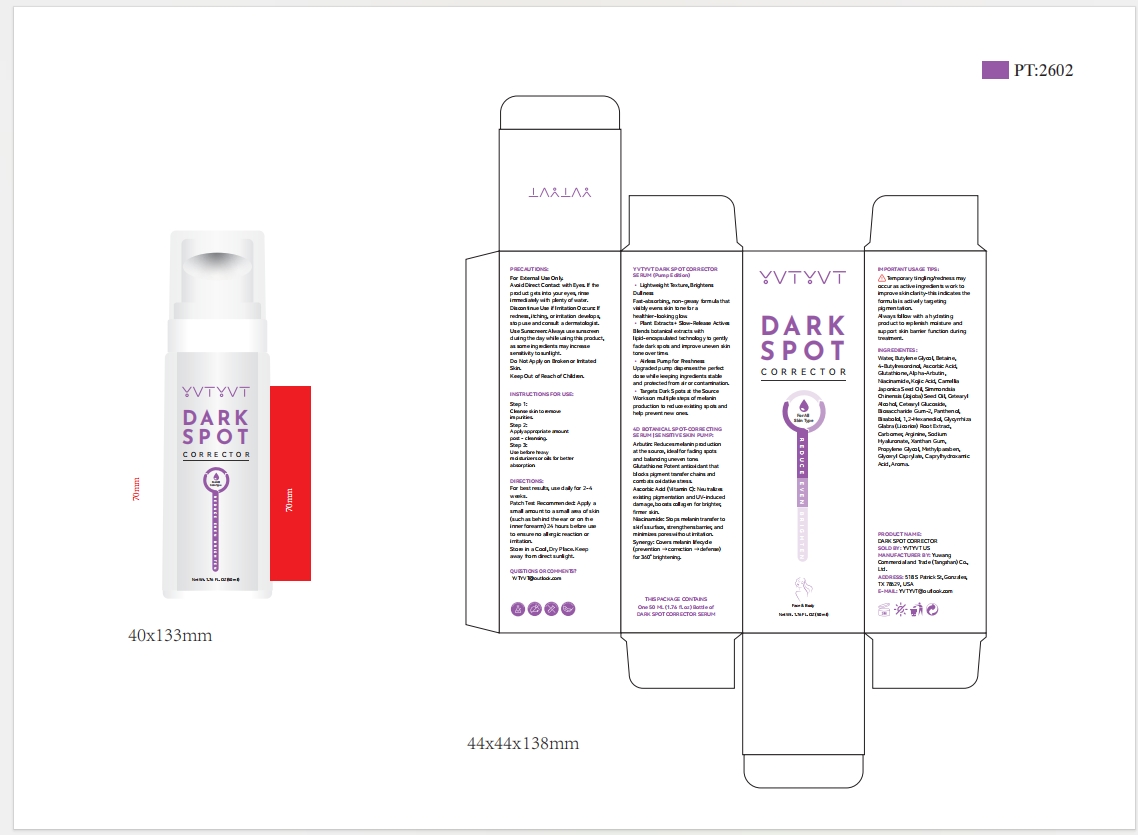 DRUG LABEL: YVTYVT DARK SPOT CORRECTOR
NDC: 85212-0031 | Form: CREAM
Manufacturer: Beijing JUNGE Technology Co., Ltd.
Category: otc | Type: HUMAN OTC DRUG LABEL
Date: 20250428

ACTIVE INGREDIENTS: SQUALANE 3 g/100 mL; NIACINAMIDE 2 g/100 mL
INACTIVE INGREDIENTS: GLYCERYL CAPRYLATE 0.1 mL/100 mL; SODIUM HYALURONATE 0.1 mL/100 mL; GLYCERIN 5 mL/100 mL; BUTYROSPERMUM PARKII (SHEA) BUTTER 2 mL/100 mL; VITAMIN E POLYETHYLENE GLYCOL SUCCINATE 1 mL/100 mL; ETHYLHEXYL PALMITATE 3 g/100 mL; LYCIUM CHINENSE ROOT BARK 0.5 mL/100 mL; GLYCYRRHIZA URALENSIS ROOT 0.5 mL/100 mL; CENTELLA ASIATICA LEAF 0.2 mL/100 mL; CAPRYLHYDROXAMIC ACID 0.1 mL/100 mL; AQUA 66.3 mL/100 mL; BUTYLENE GLYCOL 5 mL/100 mL; PANTOTHENIC ACID 0.2 mL/100 mL; SALVIA MILTIORRHIZA ROOT 0.5 mL/100 mL; HYDROLYZED ELASTIN 0.1 mL/100 mL; HYALURONIC ACID 1 mL/100 mL; 3-O-ETHYL ASCORBIC ACID 1 mL/100 mL; CETEARYL ALCOHOL 2 mL/100 mL; CARBOMER 0.1 mL/100 mL; DIPOTASSIUM GLYCYRRHIZATE 0.1 mL/100 mL; RETINOL 0.2 mL/100 mL; HELIANTHUS ANNUUS (SUNFLOWER) SEED OIL 3 mL/100 mL; PANTHENOL 1 mL/100 mL; TRANEXAMIC ACID 2 mL/100 mL

ALARMS

For External Use Only.
Avoid Direct Contact with Eyes. If the product gets into your eyes, rinse immediately with plenty of water.
Discontinue Use if Irritation Occurs: If redness, itching, or irritation develops, stop use and consult a dermatologist.
Use Sunscreen: Always use sunscreen during the day while using this product, as some ingredients may increase sensitivity to sunlight.
Do Not Apply on Broken or Irritated Skin.
Keep Out of Reach of Children.

Keep Out of Reach of Children.

STORAGE AND HANDLING

Store in a Cool, Dry Place. Keep away from direct sunlight.

DOSAGE AND ADMINISTRATION

Use Sunscreen: Always use sunscreen during the day while using this product, as some ingredients may increase sensitivity to sunlight.

WHEN USING

For best results, use daily for 2-4 weeks.

STOP USE

Avoid Direct Contact with Eyes. If the product gets into your eyes, rinse immediately with plenty of water.
Discontinue Use if Irritation Occurs: If redness, itching, or irritation develops, stop use and consult a dermatologist.

Do Not Apply on Broken or Irritated Skin.
Keep Out of Reach of Children.

ACTIVE INGREDIENT

SQUALANE
NIACINAMIDE

WARNINGS

PRECAUTIONS:
For External Use Only.
Avoid Direct Contact with Eyes. If the product gets into your eyes, rinse immediately with plenty of water.
Discontinue Use if Irritation Occurs: If redness, itching, or irritation develops, stop use and consult a dermatologist.
Use Sunscreen: Always use sunscreen during the day while using this product, as some ingredients may increase sensitivity to sunlight.
Do Not Apply on Broken or Irritated Skin.
Keep Out of Reach of Children.

INDICATIONS AND USAGE

1: Cleanse skin to remove impurities.
2: Apply appropriate amount post - cleansing.
3: Use before heavy moisturizers or oils for better absorption.

PURPOSE

DARK SPOT CORRECTOR

INACTIVE INGREDIENT

Aqua, Glycerin, Helianthus Annuus (Sunflower) Seed Oil, Butyrospermum Parkii (Shea Butter), Centella Asiatica Root Extract, Vitamin C, Hydrolyzed Hyaluronic Acid, Panthenol, Vitamin E, Phragmites Communis Extract, Salvia Miltiorrhiza Root Extract, Lycium Chinense Root Extract, Glycyrrhiza Uralensis (Licorice) Root Extract, Vitamin B5, Retinol, Symphytum Officinale Extract, Sodium Hyaluronate, Hydrolyzed Elastin